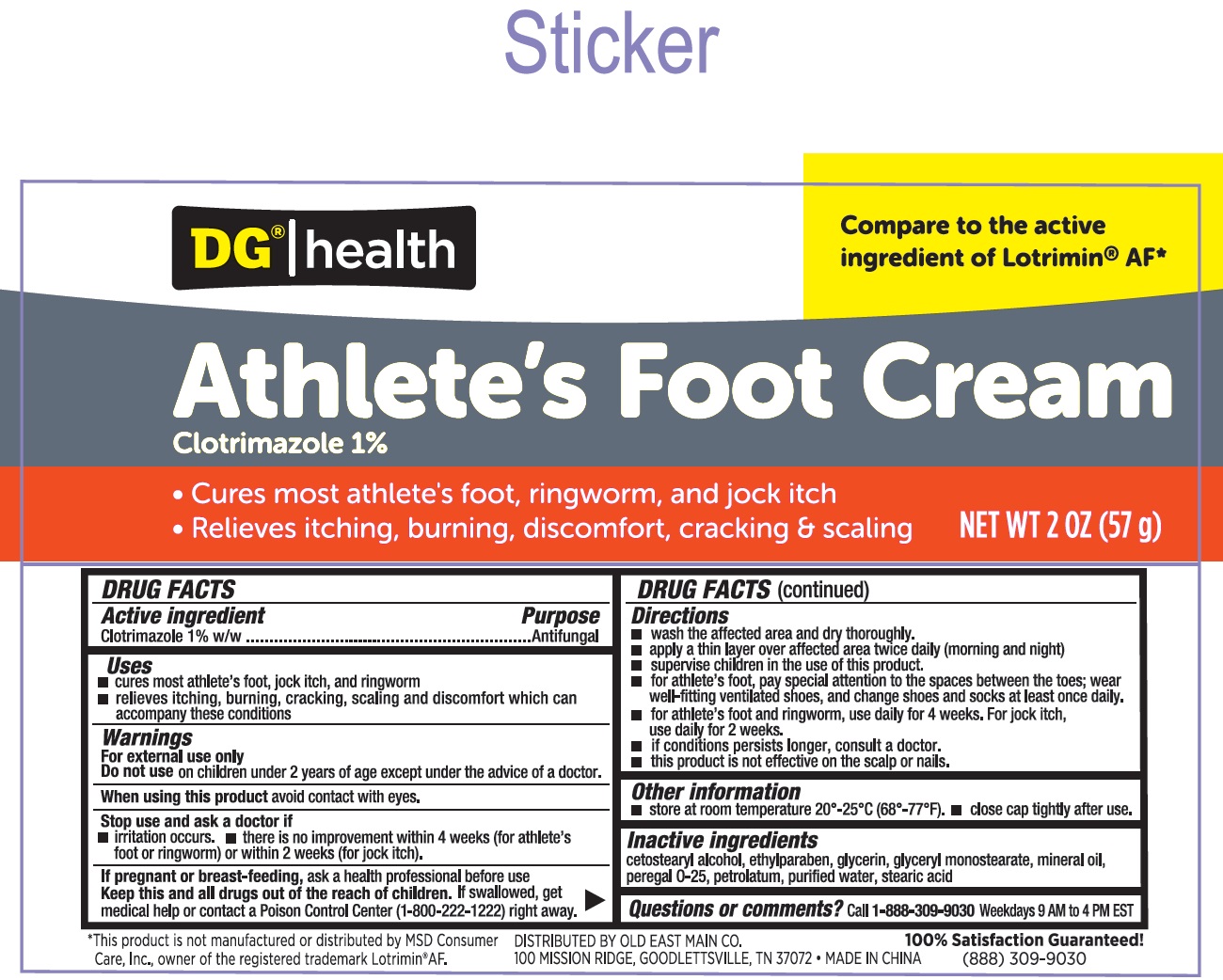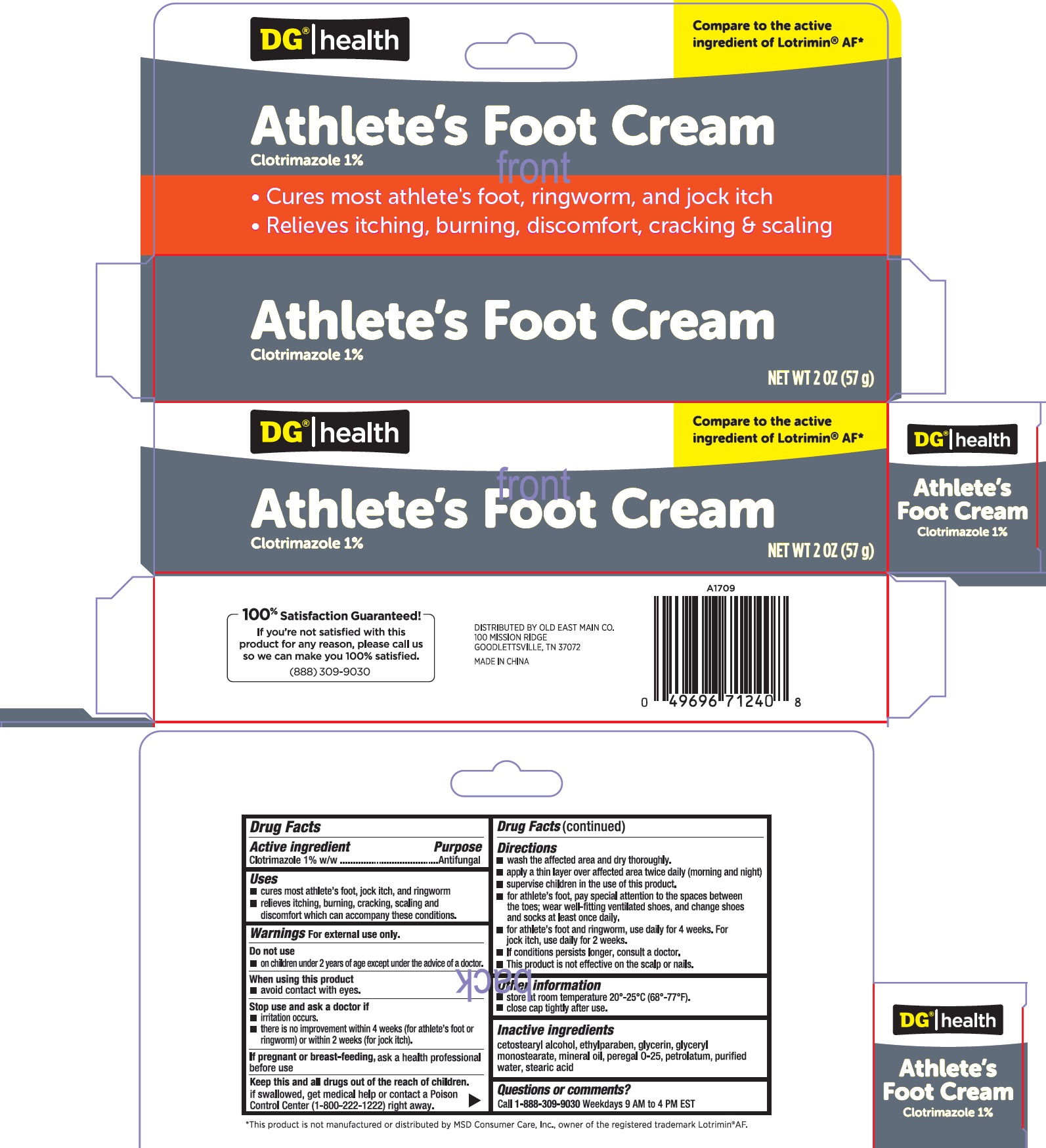 DRUG LABEL: DG Health Athletes Foot
NDC: 55910-118 | Form: CREAM
Manufacturer: Dolgencorp, Inc.
Category: otc | Type: HUMAN OTC DRUG LABEL
Date: 20250228

ACTIVE INGREDIENTS: CLOTRIMAZOLE 10 mg/1 g
INACTIVE INGREDIENTS: ETHYLPARABEN; GLYCERIN; GLYCERYL MONOSTEARATE; MINERAL OIL; PETROLATUM; CETOSTEARYL ALCOHOL; WATER; STEARIC ACID

DG Health Athlete's Foot Cream

Active ingredient

Clotrimazole 1% w/w

Purpose

Antifungal

Uses

- cures most athlete's foot, jock itch, and ringworm
- relieves itching, burning, cracking, scaling and discomfort which can accompany these conditions.

Warnnings

For external use only.

Do not use

- on children under 2 years of age except under the advice of a doctor.

When using this product

- avoid contact with eyes.

Stop use and ask a doctor if

- irritation occurs.
- there is no improvement within 4 weeks (for athlete's foot or ringworm) or within 2 weeks (for jock itch).

If pregnant or breast-feeding,

ask a health professional before use

Keep this and all drugs out of the reach of children.

if swallowed, get medical help or contact a Poison Control Center (1-800-222-1222) right away.

Directions

- wash the affected area and dry thoroughly.
- apply a thin layer over affected area twice daily (morning and night)
- supervise children in the use of this product.
- for athlete's foot, pay special attention to the spaces between the toes; wear well-fitting ventilated shoes, and change shoes and socks at least once daily.
- for athlete's foot and ringworm, use daily for 4 weeks. For jock itch, use daily for 2 weeks.
- if conditions persists longer, consult a doctor.
- This product is not effective on the scalp or nails.

Other information

- store at room temperature 20º-25ºC (68º-77ºF).
- close cap tightly after use.

Inactive ingredients

cetostearyl alcohol, ethylparaben, glycerin, glyceryl monostearate, mineral oil, peregal 0-25, petrolatum, purified water, stearic acid

Questions or comments?

Call 1-888-309-9030Weekdays 9 AM to 4 PM EST